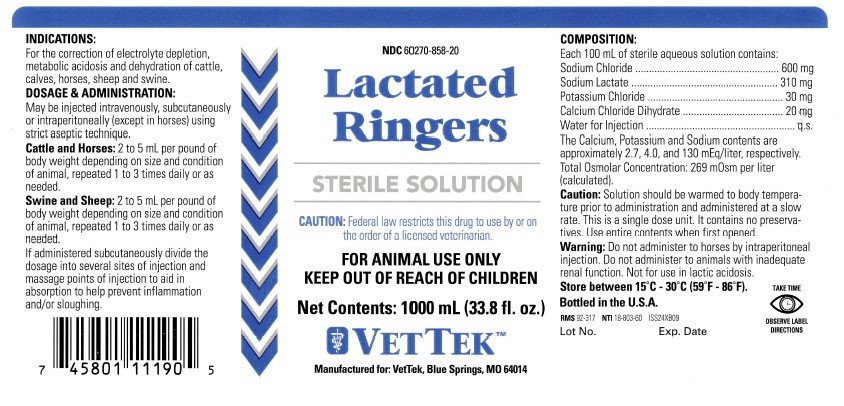 DRUG LABEL: Lactated Ringers
NDC: 60270-858 | Form: INJECTION, SOLUTION
Manufacturer: VetTek
Category: animal | Type: PRESCRIPTION ANIMAL DRUG LABEL
Date: 20250826

ACTIVE INGREDIENTS: SODIUM CHLORIDE 600 mg/100 mL; SODIUM LACTATE 310 mg/100 mL; POTASSIUM CHLORIDE 30 mg/100 mL; CALCIUM CHLORIDE 20 mg/100 mL

LACTATED RINGERS

PRECAUTIONS

TAKE TIME OBSERVE LABEL DIRECTIONS

KEEP OUT OF REACH OF CHILDREN

STERILE SOLUTION

For Animal Use Only

CAUTION: Federal law restricts this drug to use by or on the order of a licensed veterinarian.

INDICATIONS:

For the correction of electrolyte depletion, metabolic acidosis and dehydration of cattle, calves, horses, sheep and swine.

DOSAGE AND ADMINISTRATION:

May be injected intravenously, subcutaneously or intraperitoneally (except in horses) using strict aseptic technique.

Cattleand Horses: 2 to 5 mL per pound of body weight depending on size and condition of animal, repeated 1 to 3 times daily or as needed.

Swineand Sheep: 2 to 5 mL per pound of body weight depending on size and condition of animal, repeated 1 to 3 times daily or as needed.

If administered subcutaneously divide the dosage into several sites of injection and massage points of injection to aid in absorption and help prevent inflammation and/or sloughing.

STORAGE AND HANDLING

Store between 15°C - 30°C (59°F - 86°F).

INFORMATION FOR OWNERS/CAREGIVERS

NDC 60270-858-20

Bottled in the U.S.A.

RMS 92-317 NTI 18-803-60 ISS24XB09

Manufactured For: VetTek, Blue Springs,MO 64014

NET CONTENTS: 1000 mL (33.8 fl. oz.)

Lot No. Exp. Date

COMPOSITION

Each 100 mL of sterile aqueous solution contains:
Sodium Chloride..................600 mg
Sodium Lactate...................310 mg
Potassium Chloride...............30 mg
Calcium Chloride Dihydrate....20 mg
Water for Injection...................q.s.
The Calcium, Potassium and Sodium contents are approximately 2.7, 4.0, and 130 mEq/liter, respectively.
Total Osmolar Concentration: 269 mOsm per liter (calculated).

CAUTION:

Solution should be warmed to body temperature prior to administration and administered at a slow rate. This is a single dose unit. It contains no preservatives. Use entire contents when first opened.

WARNING:

Do not administer to horses by intraperitoneal injection. Do not administer to animals with inadequate renal function. Not for use in lactic acidosis.